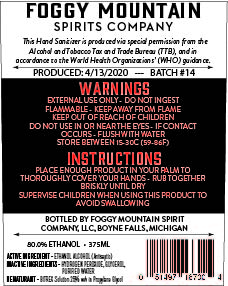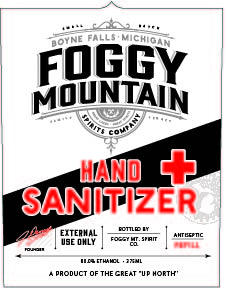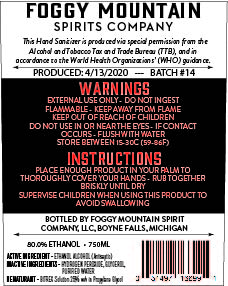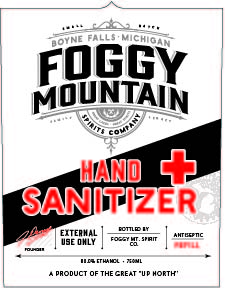 DRUG LABEL: Hand Sanitizer
NDC: 74914-001 | Form: LIQUID
Manufacturer: Foggy Mountain Spirit Company
Category: otc | Type: HUMAN OTC DRUG LABEL
Date: 20200518

ACTIVE INGREDIENTS: ALCOHOL 80 mL/100 mL
INACTIVE INGREDIENTS: GLYCERIN 1.45 mL/100 mL; HYDROGEN PEROXIDE 0.125 mL/100 mL; WATER

This is a hand sanitizer manufactured according to the Temporary Policy for Preparation of Certain Alcohol-Based Hand Sanitizer Products During the Public Health Emergency (CoViD-19); Guidance for Industry.

The hand sanitizer is manufactured using only the following United States Pharmacopoeia (USP) grade ingredients in the preparation of the product (percentage in final product formulation) consistent with World Health Organization (WHO) recommendations:

1. Alcohol (ethanol) (USP or Food Chemical Codex (FCC) grade) (80%, volume/volume (v/v)) in an aqueous solution denatured according to Alcohol and Tobacco Tax and Trade Bureau regulations in 27 CFR part 20.
2. Glycerol (1.45% v/v).
3. Hydrogen peroxide (0.125% v/v).
4. Sterile distilled water or boiled cold water.

The firm does not add other active or inactive ingredients. Different or additional ingredients may impact the quality and potency of the product.

375 sani back FDA.jpg

375 sani front FDA.jpg

750 sani back FDA.jpg

750 sani front FDA.jpg

Active Ingredient(s)

Alcohol 80% v/v. Purpose: Antiseptic

Purpose

Antiseptic, Hand Sanitizer

Use

Antiseptic Refill

Warnings

External use only. Do Not Ingest. Flammable. Keep away from flame. Keep Out Of Reach of Children. Do Not Use In or Near The Eyes. If Conatct Occurs Flush With Water.

Stop use and ask a doctor if irritation or rash occurs. These may be signs of a serious condition.

Keep out of reach of children.

Directions

- Place enough product in palm to thoroughly cover your hands. Rub together briskly until dry.
- Supervise children when using this product to avoid swallowing.

Other information

- Store between 15-30C (59-86F)

Inactive ingredients

glycerin, hydrogen peroxide, purified water, BITREX (denaturant)

Package Label - Principal Display Panel

375 mL NDC: 74914-001-01

750 mL NDC: 74914-001-02